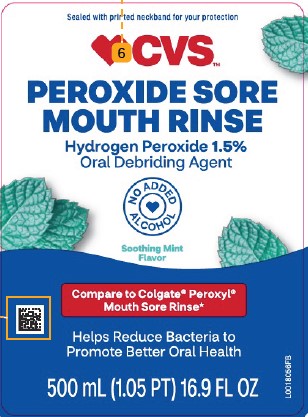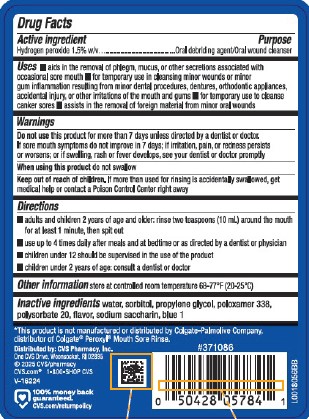 DRUG LABEL: Sore Mouth Cleanser
NDC: 69842-008 | Form: MOUTHWASH
Manufacturer: CVS Pharmacy, Inc.
Category: otc | Type: HUMAN OTC DRUG LABEL
Date: 20260203

ACTIVE INGREDIENTS: HYDROGEN PEROXIDE 150 mg/10 mL
INACTIVE INGREDIENTS: WATER; SORBITOL; PROPYLENE GLYCOL; POLOXAMER 338; POLYSORBATE 20; SACCHARIN SODIUM; FD&C BLUE NO. 1

CVS 462.002/462AA rev 1
Alcohol-Free Mint Peroxide Rinse

Active Ingredient

Hydrogen peroxide 1.5% w/v

Purpose

Oral debriding agent/Oral wound cleanser

Uses

- aids in the removal of phlegm, mucus, or other secretions associated with occasional sore mouth
- for temporary use in cleansing minor wounds or minor gum inflammation resulting from minor dental procedures, dentures, orthodontic appliances, accidental injury, or other irritations of the mouth and gums
- for temporary use to cleanse canker sores
- assists in the removal of foreign material from minor oral wounds

Warnings

For this product

Do not use

this product for more than 7 days unless directed by a dentist or doctor. If sore mouth symptoms do not improve in 7 days: if irritation, pain, or redness persists or worsens; or if swelling, rash or fever develops, see your dentist or doctor promptly

When using this product

do not swallow.

Keep out of reach of children.

If more than used for rinsing is accidentally swallowed, get medical help or contact a Poison Control Center right away.

Directions

- adults and children 2 years of age and older: rinse two teaspoons (10 mL) around the mouth for at least 1 minute, then spit out
- use up to 4 times daily after meals and at bedtime or as directed by a dentist or physician
- children under 12 should be supervised in the use of the product
- children under 2 years of age: consult a dentist or doctor

other information

store at controlled room temperature 68-77°F (20-25°C).

inactive ingredients

water, sorbitol, propylene glycol, poloxamer 338, polysorbate 20, flavor, sodium saccharin, blue 1

Disclaimer

*This product is not manufactured or distributed by Colgate-Palmolive Company, distributor of Colgate®Peroxyl®Mouth Sore Rinse.

Adverse Reactions

Distributed by: CVS Pharmacy, Inc.

One CVS Drive, Woonsocket, RI 02895

©2025 CVS/Pharmacy CVS.com 1-800-SHOP CVS

100% money back guaranteed.

CVS.com/returnpolicy

Principal display panel

Sealed with printed neckband for your protection.

CVS™

Peroxide Sore

Mouth Rinse

HYDROGEN PEROXIDE 1.5%

Oral Debriding Agent

NO ADDED ALCOHOL

Soothing Mint Flavor

Compare to Colgate®Peroxyl®Mouth Sore Rinse*

Helps reduce bacteria to promote better oral health

500 mL (1.05 PT) 16.9 FL OZ